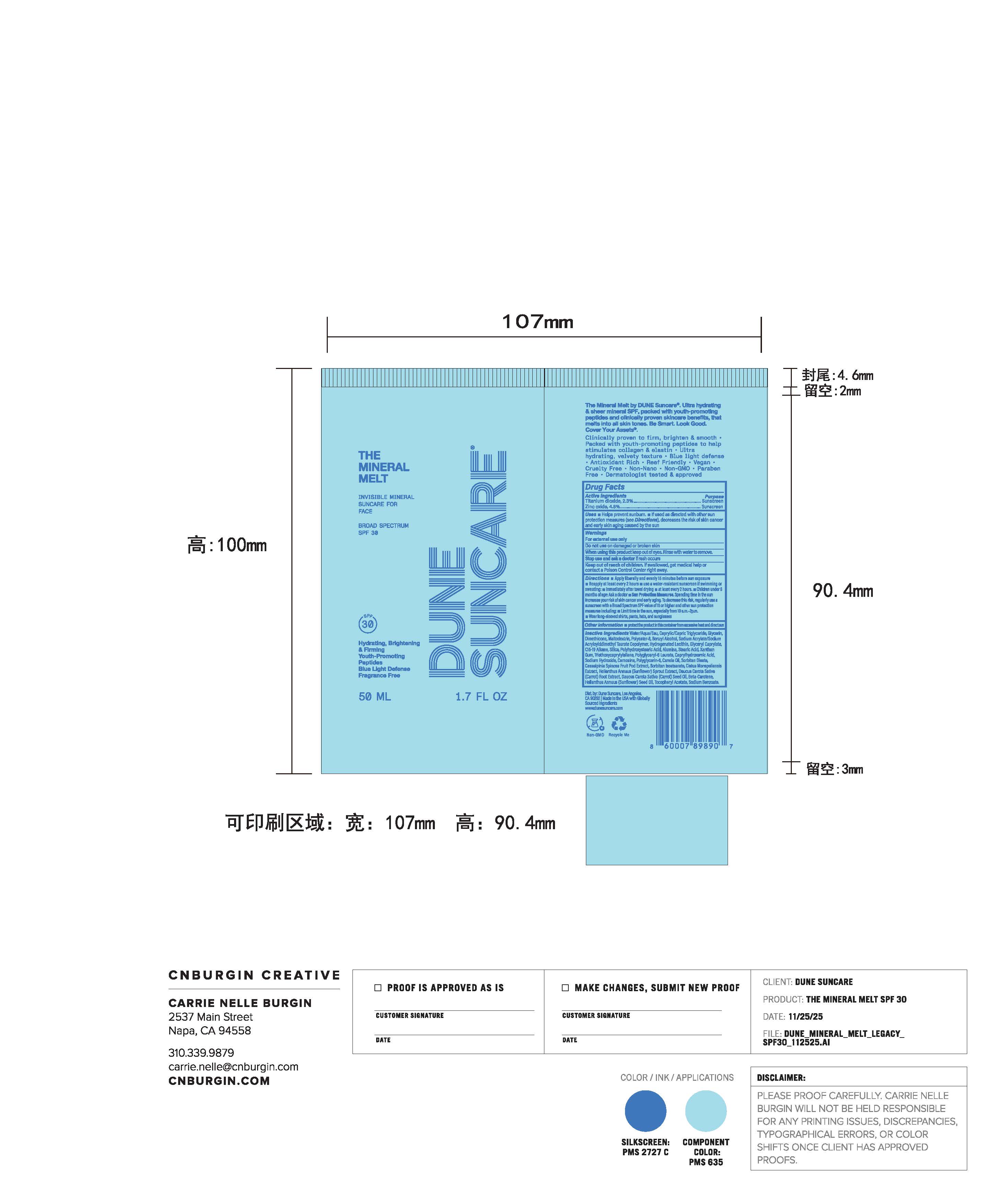 DRUG LABEL: THE MINERAL MELT
NDC: 82757-203 | Form: LOTION
Manufacturer: Dune Suncare, Inc.
Category: otc | Type: HUMAN OTC DRUG LABEL
Date: 20251219

ACTIVE INGREDIENTS: TITANIUM DIOXIDE 23 mg/1 mL; ZINC OXIDE 48 mg/1 mL
INACTIVE INGREDIENTS: HELIANTHUS ANNUUS SPROUT; DIMETHICONE; SODIUM HYDROXIDE; SILICA, TRIMETHYLSILYL CAPPED; STEARIC ACID; CISTUS MONSPELIENSIS WHOLE; SODIUM ACRYLATE/SODIUM ACRYLOYLDIMETHYLTAURATE COPOLYMER (4000000 MW); BETA-CAROTENE; CAPRYLIC/CAPRIC TRIGLYCERIDE; POLYHYDROXYSTEARIC ACID (2300 MW); CAPRYLHYDROXAMIC ACID; SORBITAN ISOSTEARATE; BENZYL ALCOHOL; GLYCERYL CAPRYLATE; HELIANTHUS ANNUUS (SUNFLOWER) SEED OIL; CARNOSINE; CANOLA OIL; ALUMINA; XANTHAN GUM; POLYGLYCERIN-6; SORBITAN OLEATE; .ALPHA.-TOCOPHEROL ACETATE, DL-; SODIUM BENZOATE; WATER; HYDROGENATED SOYBEAN LECITHIN; MALTODEXTRIN; C15-19 ALKANE; TRIETHOXYCAPRYLYLSILANE; CAESALPINIA SPINOSA FRUIT POD; POLYESTER-8 (1400 MW, CYANODIPHENYLPROPENOYL CAPPED); POLYGLYCERYL-6 LAURATE; DAUCUS CAROTA SATIVA (CARROT) SEED OIL; GLYCERIN; DAUCUS CAROTA SATIVA (CARROT) JUICE

THE MINERAL MELT

Active Ingredients

Titanium Dioxide 2.3%

Zinc Oxide 4.8%

Purpose

Sunscreen

Uses

- helps prevent sunburn
- If used as directed with other sun protection measures (see Directions), decreases the risk of skin cancer and early skin aging caused by the sun

Warnings

For external use only

Do not use

on damaged or broken skin

When using this product

keep out of eyes. Rinse with water to remove.

Stop use and ask a doctor

if rash occurs

Keep out of reach of children.

If swallowed, get medical help or contact a Poison Control Center right away.

Directions

- apply liberally and evenly 15 minutes before sun exposure
- reapply:
  - after 40 minutes of swimming or sweating
  - at least every 2 hours
  - children under 6 months: Ask a doctor
- Sun Protection Measures.Spending time in the sun increases your risk of skin cancer and early aging. To decrease this risk, regularly use a sunscreen with Broad Spectrum SPF value of 15 or higher and other sun protection measures including:
- limit time in the sun, especially from 10 a.m.–2 p.m.
- wear long-sleeve shirts, pants, hats, and sunglasses

Other information

- protect the product in this container from excessive heat and direct sun

Inactive ingredients

Water/Aqua/Eau, Caprylic/Capric Triglyceride, Glycerin, Dimethicone, Maltodextrin, Polyester-8, Benzyl Alcohol, Sodium Acrylate/Sodium Acryloyldimethyl Taurate Copolymer, Hydrogenated Lecithin, Glyceryl Caprylate, C15-19 Alkane, Silica, Polyhydroxystearic Acid, Alumina, Stearic Acid, Xanthan Gum, Triethoxycaprylylsilane, Polyglyceryl-6 Laurate, Caprylhydroxamic Acid, Sodium Hydroxide, Carnosine, Polyglycerin-6, Canola Oil, Sorbitan Oleate, Caesalpinia Spinosa Fruit Pod Extract, Sorbitan Isostearate, Cistus Monspeliensis Extract, Helianthus Annuus (Sunflower) Sprout Extract, Daucus Carota Sativa (Carrot) Root Extract, Daucus Carota Sativa (Carrot) Seed Oil, Beta-Carotene, Helianthus Annuus (Sunflower) Seed Oil, Tocopheryl Acetate, Sodium Benzoate.

Principal Display Panel

DUNE SUNCARE

THE
MINERAL
MELT

INVISIBLE MINERAL

SUNCARE FOR

FACE

BROAD SPECTRUM

SPF 30

Hydrating, Brightening

& FIrming

Youth-Promoting

Peptides

Blue Light Defense

Fragrance Free

50 mL

1.7 FL OZ